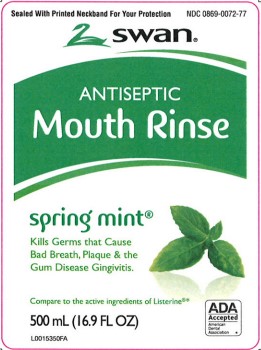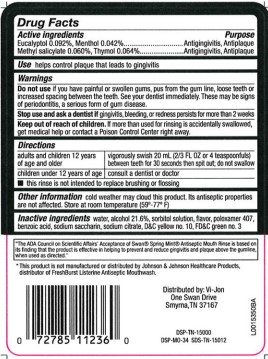 DRUG LABEL: Antiseptic
NDC: 0869-0072 | Form: MOUTHWASH
Manufacturer: Vi Jon, LLC
Category: otc | Type: HUMAN OTC DRUG LABEL
Date: 20260116

ACTIVE INGREDIENTS: EUCALYPTOL 0.92 mg/1 mL; MENTHOL 0.42 mg/1 mL; METHYL SALICYLATE 0.6 mg/1 mL; THYMOL 0.64 mg/1 mL
INACTIVE INGREDIENTS: WATER; ALCOHOL; SORBITOL; POLOXAMER 407; BENZOIC ACID; SACCHARIN SODIUM; SODIUM CITRATE; D&C YELLOW NO. 10; FD&C GREEN NO. 3

Swan 072.003/072AN
Spring Mint Antiseptic Mouthrinse

Active ingredients

Eucalyptol 0.092%

Menthol 0.042%

Methyl salicylate 0.060%

Thymol 0.064%

Purpose

Antigingivitis, Antiplaque

Use

helps control plaque that leads to gingivitis

Warnings

for this product

Do not use

if you have painful or swollen gums, pus from the gum line, loose teeth or increased spacing between the teeth. See your dentist immediately. These may be signs of periodontitis, a serious form of gum disease.

Stop use and ask a dentist if

gingivitis, bleeding, or redness persists for more than 2 weeks

Keep out of reach of children

If more than used for rinsing is accidentally swallowed, get medical help or contact a Poison Control Center right away.

Directions

adults and children 12 years of age and older vigorously swish 20 mL (2/3 FL OZ or 4 teaspoonfuls) between teeth for 30 seconds then spit out; do not swallow

children under 12 years of age consult a dentist or doctor

- this rinse is not intended to replace brushing or flossing

Other information

cold weather may cloud this product. Its antiseptic properties are not affected. Store at room temperature (59°-77°F).

inactive ingredents

water, alcohol 21.6%, sorbitol solution, flavor, poloxamer 407, benzoic acid, sodium saccharin, sodium citrate, D&C yellow no. 10, FD&C green no. 3

Claims

"The ADA Council on Scientific Affairs Acceptance of Swan Spring Mint Antiseptic Mouth Rinse is based on its finding that the product is effective in helping to prevent and reduce gingivitis and plaque about the gumline, when used as directed."

Disclaimer

*This product is not manufactured or distributed by Johnson & Johnson Healthcare Products, distributor FreshBurst ListerineAnitseptic Mouthwash.

Adverse reaction

Distributed By:

Vi-Jon, LLC

One Swan Drive

Smyrna, TN 37167

DSP-TN-15000

DSP-MO-34

SDS-TN-15012

Principal display panel

Sealed With Printed Neckband For Your Protection

NDC 0869-0072-77

swan®

ANTISEPTIC

Mouth Rinse

spring mint®

Kills Germs that Cause Bad Breath, Plaque & the Gum Disease Gingivitis.

Compare to the active ingredients in Listerine®*

ADA ACCEPTED

AMERICAN DENTAL ASSOCIATION

500 mL (16.9 FL OZ)